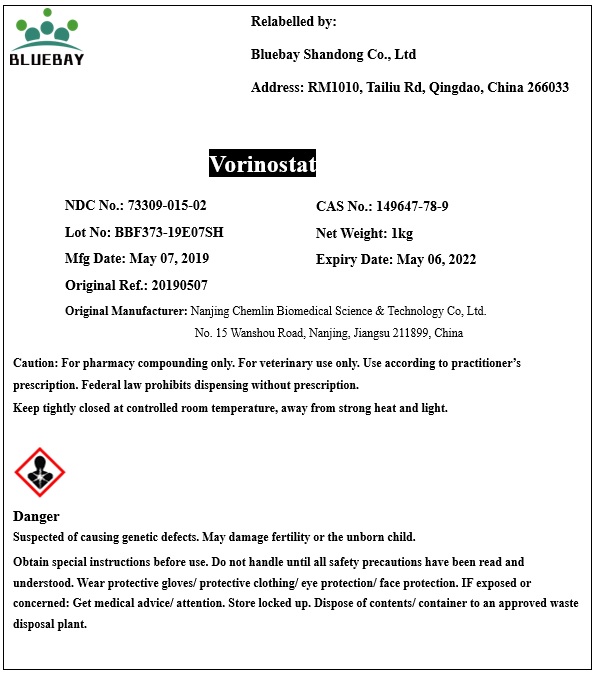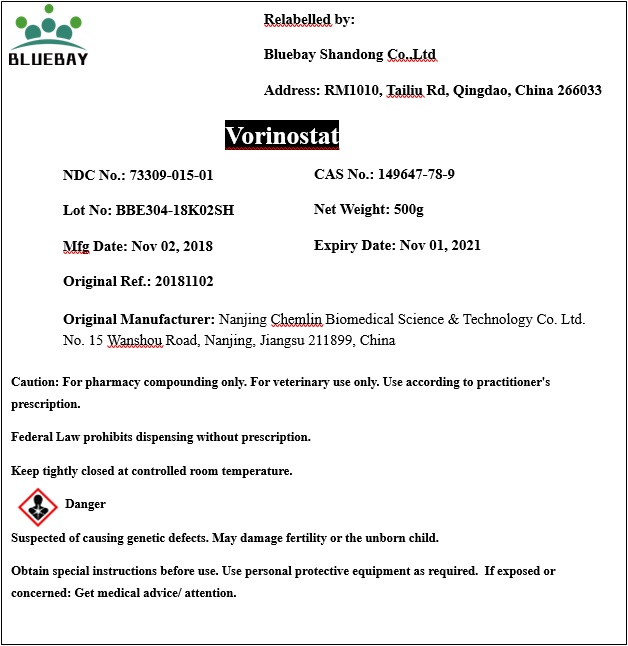 DRUG LABEL: Vorinostat
NDC: 73309-015 | Form: POWDER
Manufacturer: BLUEBAY SHANDONG CO.,LTD
Category: other | Type: BULK INGREDIENT
Date: 20200817

ACTIVE INGREDIENTS: VORINOSTAT 1 g/1 g

Vorinostat